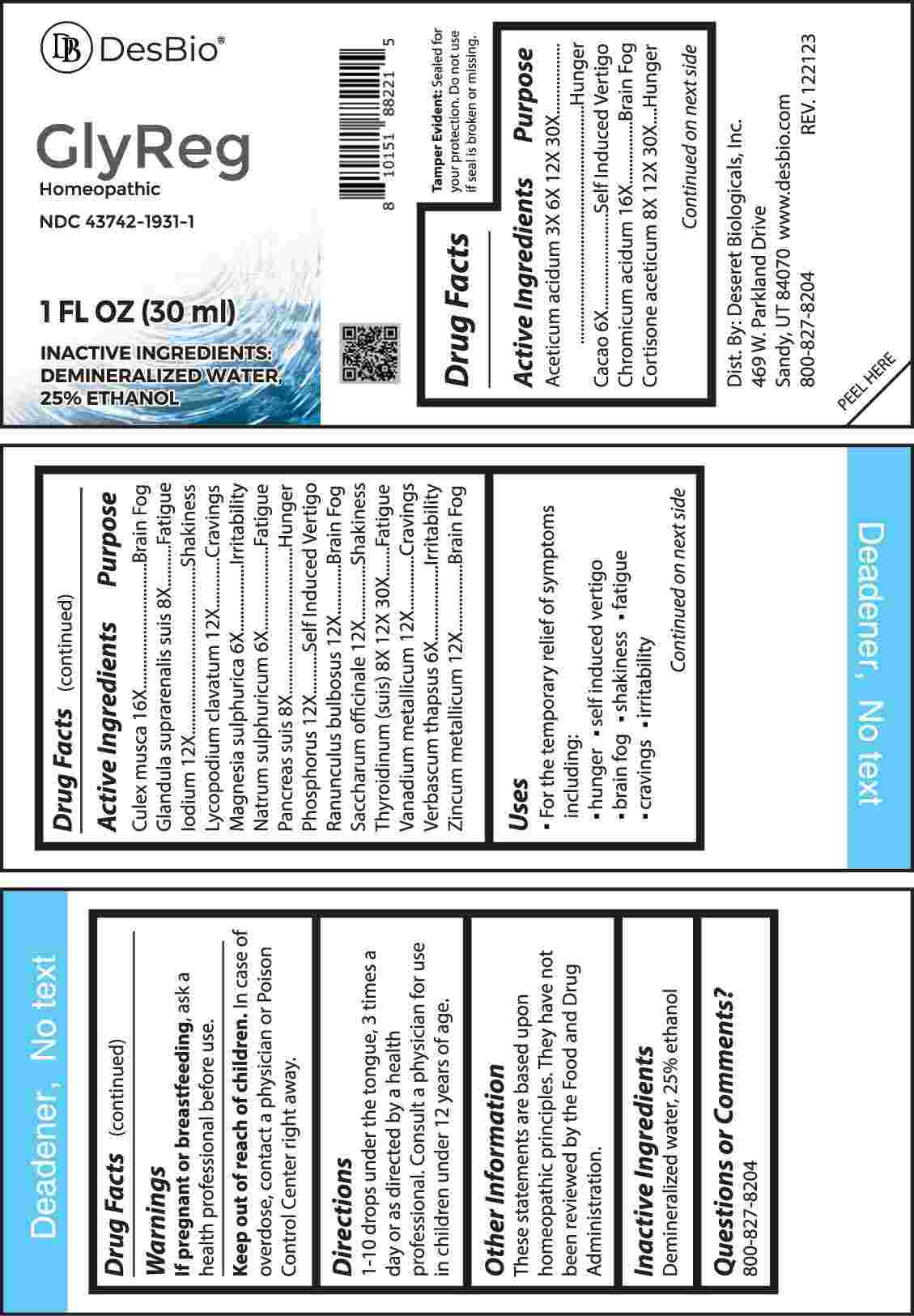 DRUG LABEL: Glyreg
NDC: 43742-1931 | Form: LIQUID
Manufacturer: Deseret Biologicals, Inc
Category: homeopathic | Type: HUMAN OTC DRUG LABEL
Date: 20240423

ACTIVE INGREDIENTS: ACETIC ACID 3 [hp_X]/1 mL; COCOA 6 [hp_X]/1 mL; MAGNESIUM SULFATE HEPTAHYDRATE 6 [hp_X]/1 mL; SODIUM SULFATE 6 [hp_X]/1 mL; VERBASCUM THAPSUS WHOLE 6 [hp_X]/1 mL; SUS SCROFA ADRENAL GLAND 8 [hp_X]/1 mL; SUS SCROFA PANCREAS 8 [hp_X]/1 mL; CORTISONE ACETATE 8 [hp_X]/1 mL; THYROID 8 [hp_X]/1 mL; IODINE 12 [hp_X]/1 mL; LYCOPODIUM CLAVATUM SPORE 12 [hp_X]/1 mL; PHOSPHORUS 12 [hp_X]/1 mL; RANUNCULUS BULBOSUS WHOLE 12 [hp_X]/1 mL; SUCROSE 12 [hp_X]/1 mL; VANADIUM 12 [hp_X]/1 mL; ZINC 12 [hp_X]/1 mL; CHROMIUM TRIOXIDE 16 [hp_X]/1 mL; CULEX PIPIENS 16 [hp_X]/1 mL
INACTIVE INGREDIENTS: WATER; ALCOHOL

DRUG FACTS:

ACTIVE INGREDIENTS:

Aceticum Acidum 3X, 6, 12X, 30X, Cacao 6X, Chromium Acidum 16X, Cortisone Aceticum 8X, 12X, 30X, Culex Musca 16X, Glandula Suprarenalis Suis 8X, Iodium 12X, Lycopodium Clavatum 12X, Magnesia Sulphurica 6X, Natrum Sulphuricum 6X, Pancreas Suis 8X, Phosphorus 12X, Ranunculus Bulbosus 12X, Saccharum Officinale 12X, Thyroidinum (Suis) 8X, 12X, 30X, Vanadium Metallicum 12X, Verbascum Thapsus 6X, Zincum Metallicum 12X.

PURPOSE:

Aceticum Acidum - Hunger, Cacao – Self Induced Vertigo, Chromium Acidum – Brain Fog, Cortisone Aceticum - Hunger, Culex Musca – Brain Fog, Glandula Suprarenalis Suis - Fatigue, Iodium - Shakiness, Lycopodium Clavatum - Cravings, Magnesia Sulphurica - Irritability, Natrum Sulphuricum - Fatigue, Pancreas Suis - Hunger, Phosphorus – Self Induced Vertigo, Ranunculus Bulbosus – Brain Fog, Saccharum Officinale - Shakiness, Thyroidinum (Suis) - Fatigue, Vanadium Metallicum - Cravings, Verbascum Thapsus - Irritability, Zincum Metallicum – Brain Fog

USES:

• For the temporary relief of symptoms including:

• hunger • self induced vertigo • brain fog

• shakiness • fatigue • cravings • irritability

These statements are based upon homeopathic principles. They have not been reviewed by the Food and Drug Administration.

WARNINGS:

If pregnant or breast-feeding, ask a health professional before use.

Keep out of reach of children. In case of overdose, contact a physician or Poison Control Center right away.

Tamper Evident: Sealed for your protection. Do not use if seal is broken or missing.

KEEP OUT OF REACH OF CHILDREN:

In case of overdose, contact a physician or Poison Control Center right away.

DIRECTIONS:

1-10 drops under the tongue, 3 times a day or as directed by a health professional. Consult a physician for use in children under 12 years of age.

INACTIVE INGREDIENTS:

Demineralized water, 25% ethanol

QUESTIONS:

Dist. By: Deseret Biologicals, Inc.
469 W. Parkland Drive
Sandy, UT 84070

www.desbio.com

800-827-8204

PACKAGE LABEL DISPLAY:

Des Bio

GlyReg

Homeopathic
NDC 43742-1931-1
1 FL OZ (30 ml)